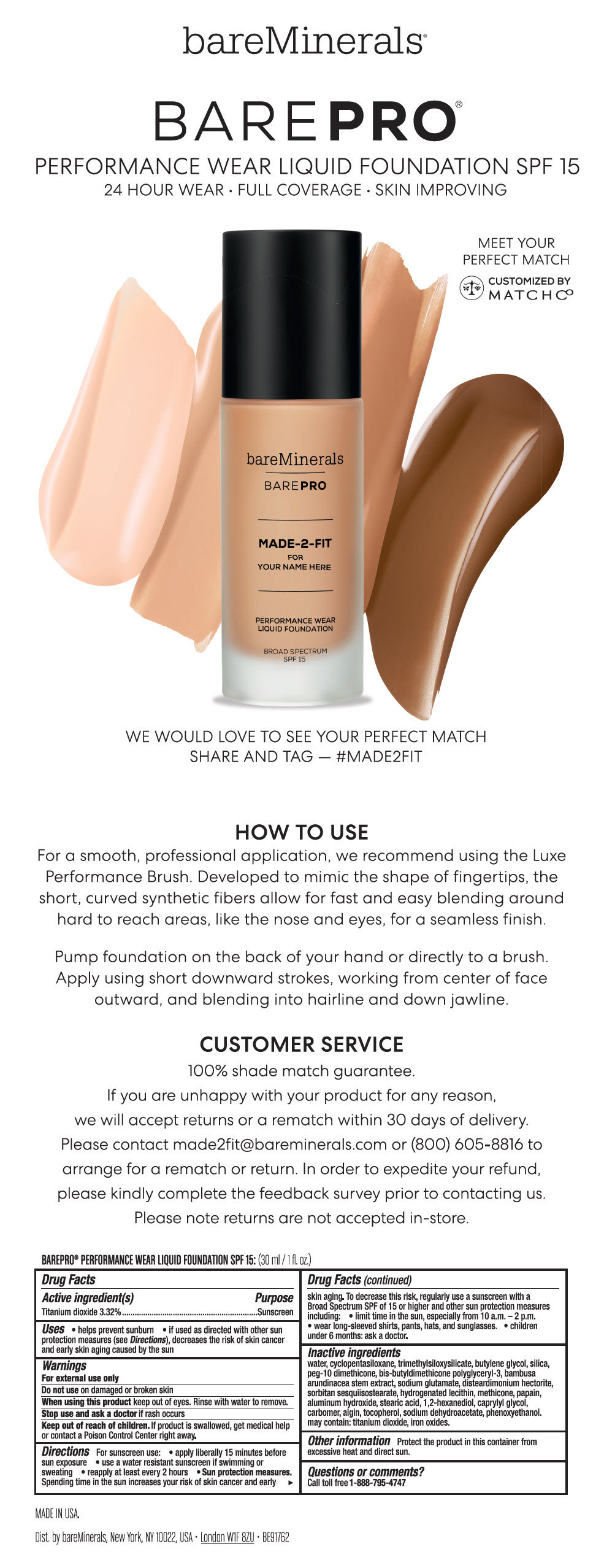 DRUG LABEL: bareMinerals BarePRO Made-2-Fit Performance Wear Foundation Broad Spectrum SPF 15
NDC: 98132-253 | Form: LIQUID
Manufacturer: Bare Escentuals Beauty, Inc.
Category: otc | Type: HUMAN OTC DRUG LABEL
Date: 20190201

ACTIVE INGREDIENTS: Titanium Dioxide 33.2 mg/1 mL
INACTIVE INGREDIENTS: Water; CYCLOMETHICONE 5; Butylene Glycol; SILICON DIOXIDE; PEG-10 DIMETHICONE (600 CST); BAMBUSA BAMBOS STEM; MONOSODIUM GLUTAMATE; Disteardimonium Hectorite; Sorbitan Sesquiisostearate; HYDROGENATED SOYBEAN LECITHIN; METHICONE (20 CST); Papain; Aluminum Hydroxide; Stearic Acid; 1,2-Hexanediol; Caprylyl Glycol; CARBOXYPOLYMETHYLENE; SODIUM ALGINATE; Tocopherol; Sodium Dehydroacetate; Phenoxyethanol; FERRIC OXIDE RED

bareMinerals® BarePRO® Made-2-Fit Performance Wear Liquid Foundation Broad Spectrum SPF 15

Drug Facts

Active ingredients

Titanium Dioxide 3.32%

Purpose

Sunscreen

Uses

- helps prevent sunburn
- if used as directed with other sun protection measures (see Directions), decreases the risk of skin cancer and early skin aging caused by the sun

Warnings

For external use only

Do not use on damaged or broken skin

When using this product keep out of eyes. Rinse with water to remove.

Stop use and ask a doctor if rash occurs.

Keep out of reach of children. If product is swallowed, get medical help or contact a Poison Control Center right away.

Directions

For sunscreen use:

- apply liberally 15 minutes before sun exposure
- use a water resistant sunscreen if swimming or sweating
- reapply at least every 2 hours
- children under 6 months: ask a doctor
- Sun Protection Measures. Spending time in the sun increases your risk of skin cancer and early skin aging. To decrease this risk, regularly use a sunscreen with a broad spectrum SPF of 15 or higher and other sun protection measures including:
  - limit time in the sun, especially from 10 a.m. – 2 p.m.
  - wear long-sleeve shirts, pants, hats, and sunglasses

Inactive Ingredients

water, cyclopentasiloxane, trimethylsiloxysilicate, butylene glycol, silica, peg-10 dimethicone, bis-butyldimethicone polyglyceryl-3, bambusa arundinacea stem extract, sodium glutamate, disteardimonium hectorite, sorbitan sesquiisostearate, hydrogenated lecithin, methicone, papain, aluminum hydroxide, stearic acid, 1,2-hexanediol, caprylyl glycol, carbomer, algin, tocopherol, sodium dehydroacetate, phenoxyethanol. may contain (+/-): titanium dioxide, iron oxides.

Other information

Protect this product in this container from excessive heat and direct sun.

Questions or comments?

Call toll free 1-800-795-4747

Dist. by bareMinerals, New York, NY 10022, USA

PRINCIPAL DISPLAY PANEL - 30 mL Tip Card

bareMinerals®

BAREPRO®

PERFORMANCE WEAR LIQUID FOUNDATION SPF 15
24 HOUR WEAR • FULL COVERAGE • SKIN IMPROVING

MEET YOUR
PERFECT MATCH

CUSTOMIZED BY
MATCH Co

WE WOULD LOVE TO SEE YOUR PERFECT MATCH
SHARE AND TAG — #MADE2FIT